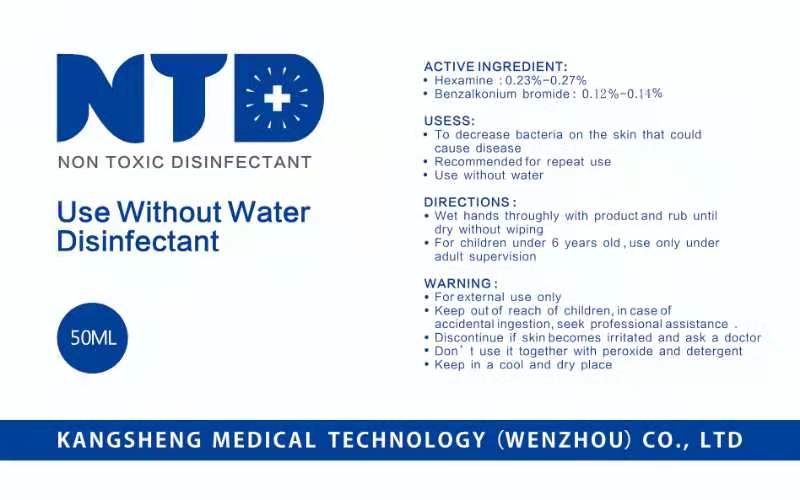 DRUG LABEL: SANITIZER
NDC: 93068-003 | Form: LIQUID
Manufacturer: KANGSHENG MEDICAL TECHNOLOGY (WENZHOU) CO. , LTD
Category: otc | Type: HUMAN OTC DRUG LABEL
Date: 20201223

ACTIVE INGREDIENTS: BENZALKONIUM 0.1 g/100 mL; METHENAMINE 0.27 g/100 mL
INACTIVE INGREDIENTS: WATER

Active Ingredient(s)

Hexamine:0.23%-0.27%

Benzalkonium bromide:0.12%-0.14%

Purpose

Antiseptic

Use

To decrease bacteria on the skin that could cause disease

recommended for repeat use

Use without water

Warnings

For external use only.

Keep out of reach of children, in case of accidental ingestion,seek professional assistance.

Discontinue if skin becomes irritated and ask a doctor

Do not use it together with peroxide and detergent

Keep in a cool and dry place

Do not use

it together with peroxide and detergent

WHEN USING

.

STOP USE

discontinue if skin becomes irritated and ask a doctor

Keep out of reach of children.in case if accidental ingestion,seek professional assistance

Directions

Wet hands throughly with product and rub until dry without wiping

For children under 6 years old,use only under adult supervision

Inactive ingredients

water